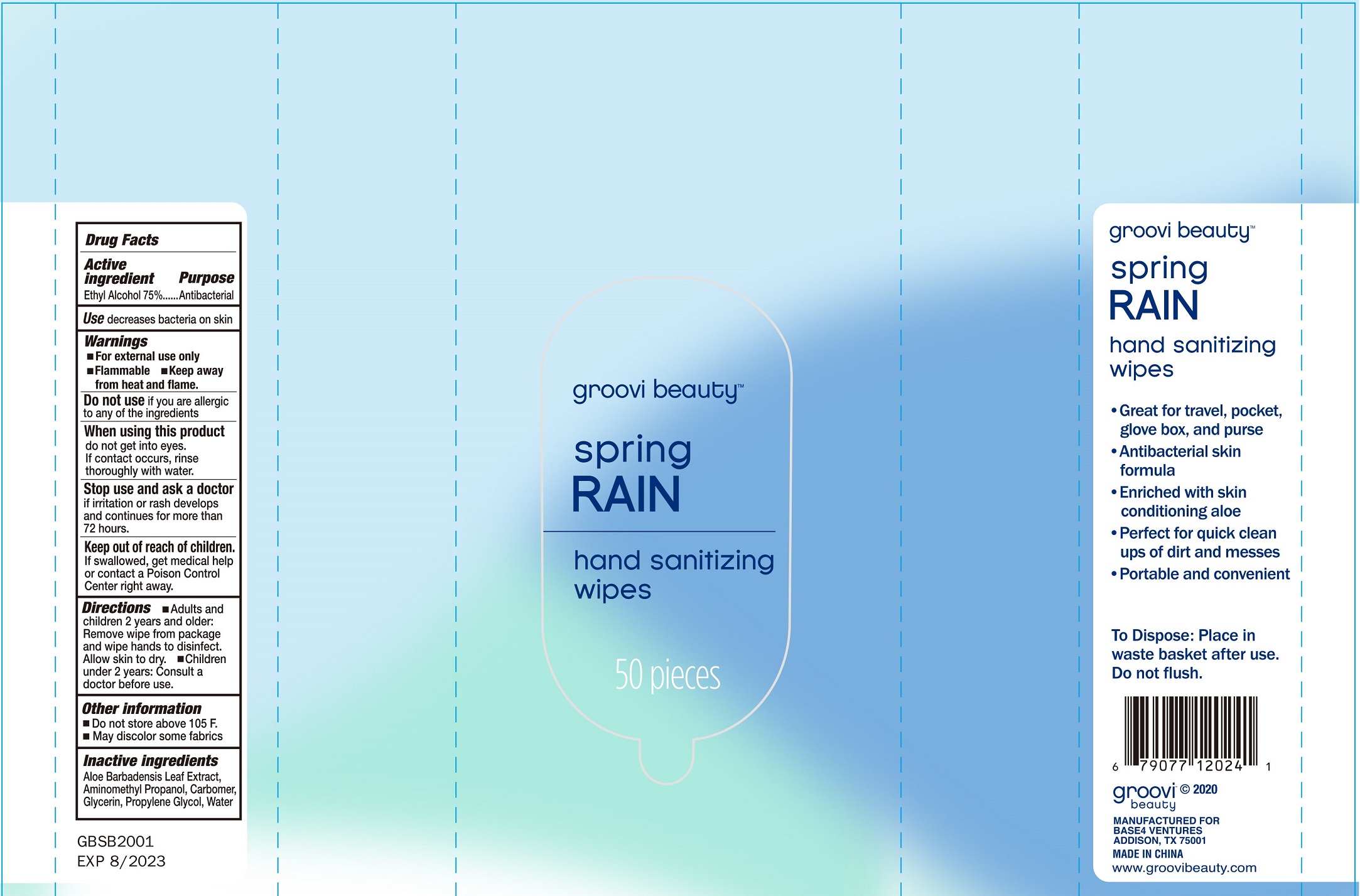 DRUG LABEL: groovi beauty spring RAIN hand sanitizing wipes
NDC: 77435-109 | Form: SWAB
Manufacturer: HAINING LILY CLEANING PRODUCTS CO., LTD
Category: otc | Type: HUMAN OTC DRUG LABEL
Date: 20200728

ACTIVE INGREDIENTS: ALCOHOL 75 g/100 g
INACTIVE INGREDIENTS: water; PROPYLENE GLYCOL; GLYCERIN; AMINOMETHYLPROPANOL; ALOE VERA LEAF

Antibacterial Wipes

Active Ingredient

Ethyl Alcohol 75%

Purpose

Antibacterial

INDICATIONS AND USAGE

decreases bacteria on skin

Warning

- For external use only.
- Flammable, keep away from heat and flame
- Do not sue if you are allergic to any of the ingredients.
- When uising this product do not get into eyes, if contact occurs, rinse thoroughly with water.
- Stop use and ask a doctor if irritation or rash develops and continues for more than 72 hours.

Do not store above 105℉.

May discolor some fabrics.

KEEP OUT OF REACH OF CHILDREN

If swallowed,, get medical help or contact a poison control center right away.

direction

- Adults and children 2 years and older: Remove wipe fro package and wipe hands to disinfect. Allow skin to dry.
- Children under 2 years: consult a doctor before use.

Inactive ingredients

Aloe Barbadensis Leaf Extract, Aminomethyl Propanol, Carbomer, Glycerin, Propylene Glycol, Water